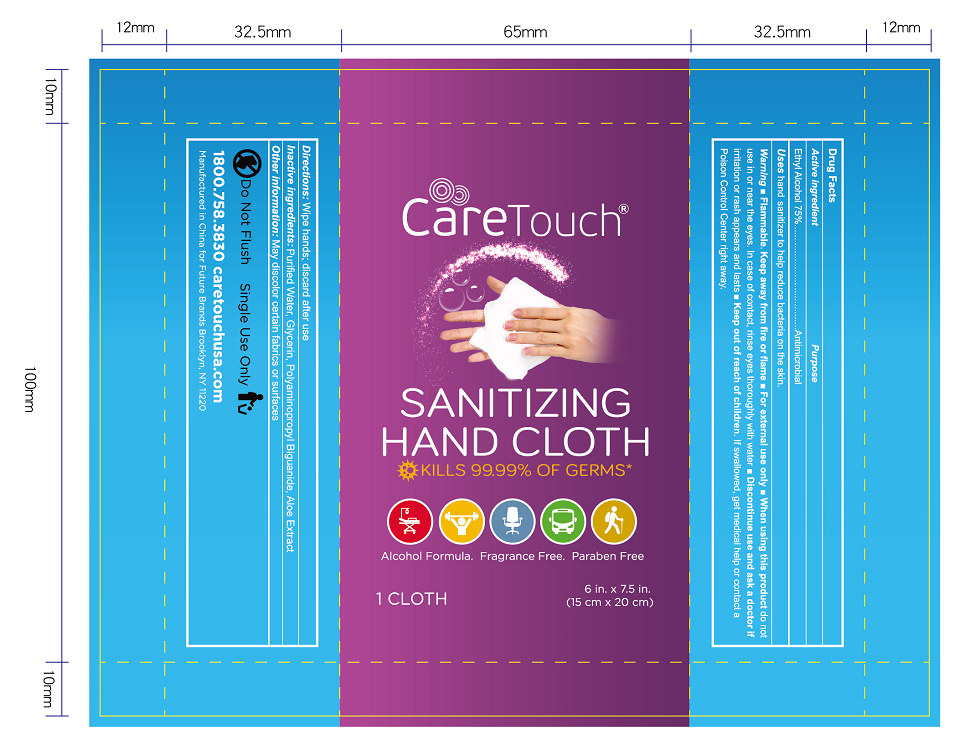 DRUG LABEL: Alcohol Wipes
NDC: 54237-019 | Form: CLOTH
Manufacturer: Guangzhou Daieme Cosmetic Co,.Ltd
Category: otc | Type: HUMAN OTC DRUG LABEL
Date: 20200814

ACTIVE INGREDIENTS: ALCOHOL 3.6 g/1 1
INACTIVE INGREDIENTS: GLYCERIN; POLYURETHANE-34 (40 MPA, TENSILE STRENGTH OF FILM AT BREAK); WATER; ALOE

DOSAGE AND ADMINISTRATION

Please use it as soon as possible after opening Place it in a cool and dry place

INACTIVE INGREDIENT

Purified Water, Glycerin, Polyurethane, Aloe Extract

INDICATIONS AND USAGE

Open the package, pull out a paper towel, wipe back and forth between palms

ACTIVE INGREDIENT

Ethyl Alcohol

keep out of reach of children

PURPOSE

Disinfection
Sterilization
No Rinseing

WARNINGS

Alcohol is volatile ,Please use it as soon as possible after opening Place it in a cool and dry place, avoid direct sunlight and fire,and avoid children eating by mistake Please keep out of the reach of children, Avoid contact with eyes and damaged skin.